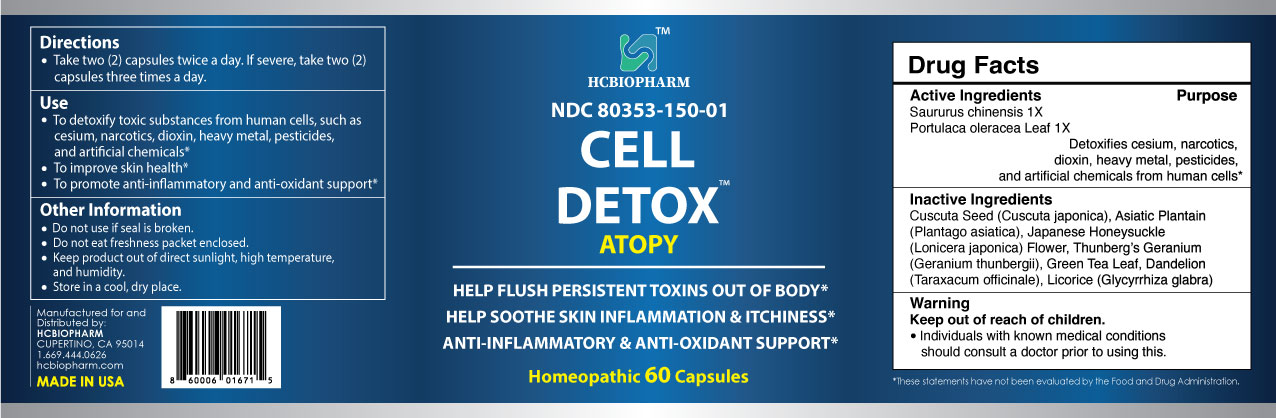 DRUG LABEL: HCBIOPHARM CELL DETOX ATOPY
NDC: 80353-150 | Form: CAPSULE
Manufacturer: HCBIOPHARM
Category: homeopathic | Type: HUMAN OTC DRUG LABEL
Date: 20250103

ACTIVE INGREDIENTS: PORTULACA OLERACEA LEAF 1 [hp_X]/1 1; SAURURUS CHINENSIS WHOLE 1 [hp_X]/1 1
INACTIVE INGREDIENTS: GREEN TEA LEAF; GERANIUM THUNBERGII WHOLE; TARAXACUM OFFICINALE; PLANTAGO ASIATICA; LONICERA JAPONICA FLOWER; CUSCUTA JAPONICA SEED; GLYCYRRHIZA GLABRA

ACTIVE INGREDIENT

Saururus chinensis 1X

Portulaca oleracea Leaf 1X

PURPOSE

Detoxifies cesium, narcotics, dioxin, heavy metal, pesticides, and artificial chemicals from human cells.*

Keep out of reach of children

DOSAGE AND ADMINISTRATION

Take two (2) capsules twice a day. If severe, take two (2) capsules three times a day.

INDICATIONS AND USAGE

To detoxify toxic substances from human cells, such as cesium, narcotics, dioxin, heavy metal, pesticides, and artificial chemicals*

To improve skin health*

To promote anti-inflammatory and anti-oxidant support*

INACTIVE INGREDIENT

Cuscuta Seed (Cuscuta japonica), Asiatic Plantain (Plantago asiatica), Japanese Honeysuckle (Lonicera japonica) Flower, Thunberg’s Geranium (Geranium thunbergii), Green Tea Leaf, Dandelion (Taraxacum officinale), Licorice (Glycyrrhiza glabra)

WARNINGS

Individuals with known medical conditions should consult a doctor prior to using this.

Do not use if seal is broken.

Do not eat freshness packet enclosed.

Keep out of direct sunlight, high temperature, and humidity.

Store in a cool, dry place.